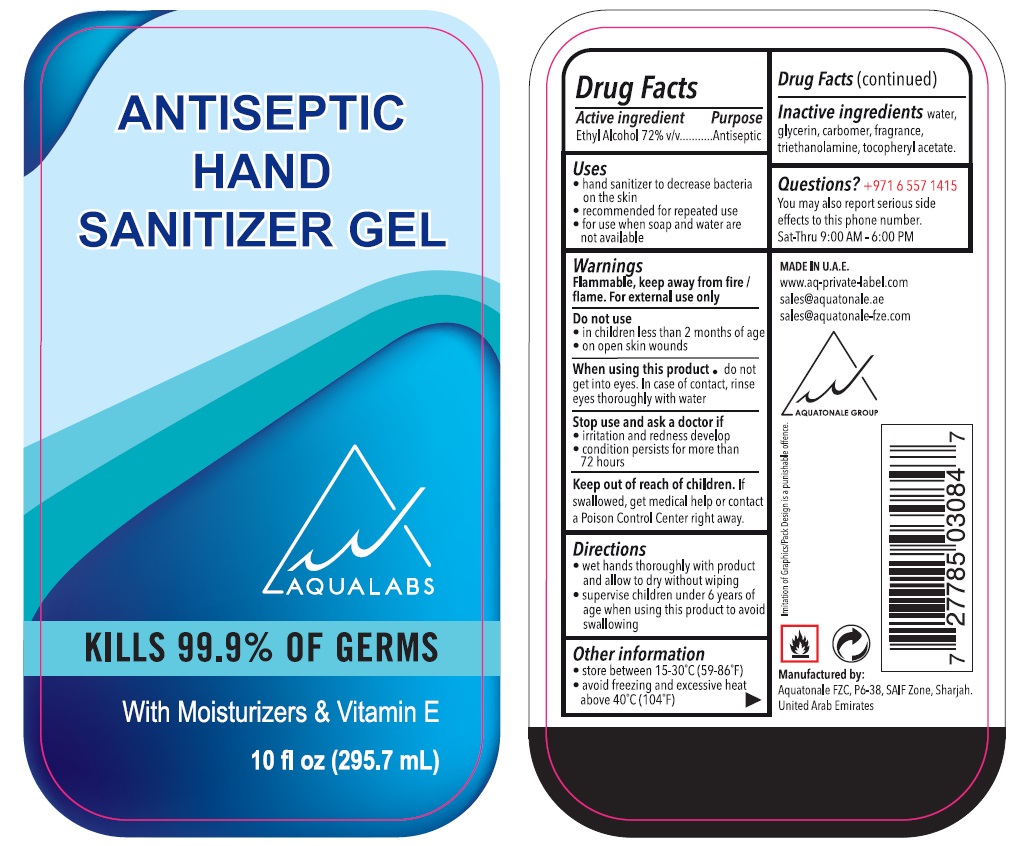 DRUG LABEL: AQUALABS ANTISEPTIC HAND SANITIZER
NDC: 80953-894 | Form: GEL
Manufacturer: Aquatonale FZC
Category: otc | Type: HUMAN OTC DRUG LABEL
Date: 20241209

ACTIVE INGREDIENTS: ALCOHOL 72 mL/100 mL
INACTIVE INGREDIENTS: WATER; GLYCERIN; CARBOMER HOMOPOLYMER, UNSPECIFIED TYPE; TROLAMINE; .ALPHA.-TOCOPHEROL ACETATE

AQUALABS ANTISEPTIC HAND SANITIZER GEL

Active ingredient

Ethyl Alcohol 72% v/v

Purpose

Antiseptic

Uses

• hand sanitizer to decrease bacteria on the skin

• recommended for repeated use

• for use when soap and water are not available

Warnings

Flammable, keep away from fire / flame. For external use only

Do not use

• in children less than 2 months of age

• on open skin wounds

When using this product • do not get into eyes. In case of contact, rinse eyes thoroughly with water

Stop use and ask a doctor if

• irritation and redness develop

• condition persists for more than 72 hours

Keep out of reach of children. If swallowed, get medical help or contact a Poison Control Center right away.

Directions

• wet hands thoroughly with product and allow to dry without wiping

• supervise children under 6 years of age when using this product to avoid swallowing

Other information

• store between 15-30°C (59-86°F)

• avoid freezing and excessive heat above 40°C (104°F)

Inactive ingredients

water, glycerin, carbomer, fragrance, triethanolamine, tocopheryl acetate.

Questions?

+ 971 6 557 1415

You may also report serious side effects to this phone number.

Sat-Thur 9:00 AM - 6:00 PM

KILLS 99.9% OF GERMS

With Moisturizers & Vitamin E

MADE IN U.A.E.

www.aq-private-label.com

sales@aquatonale.ae

sales@aquatonale-fze.com

AQUATONALE GROUP

Imitation of Graphics/Pack Design is a punishable offence.

Manufactured by:

Aquatonale FZC, P6-38, SAIF Zone, Sharjah.

United Arab Emirates